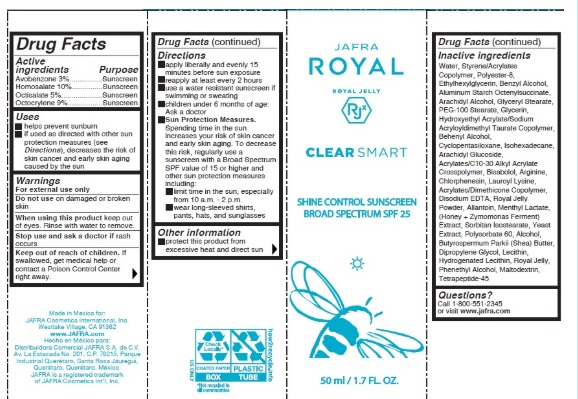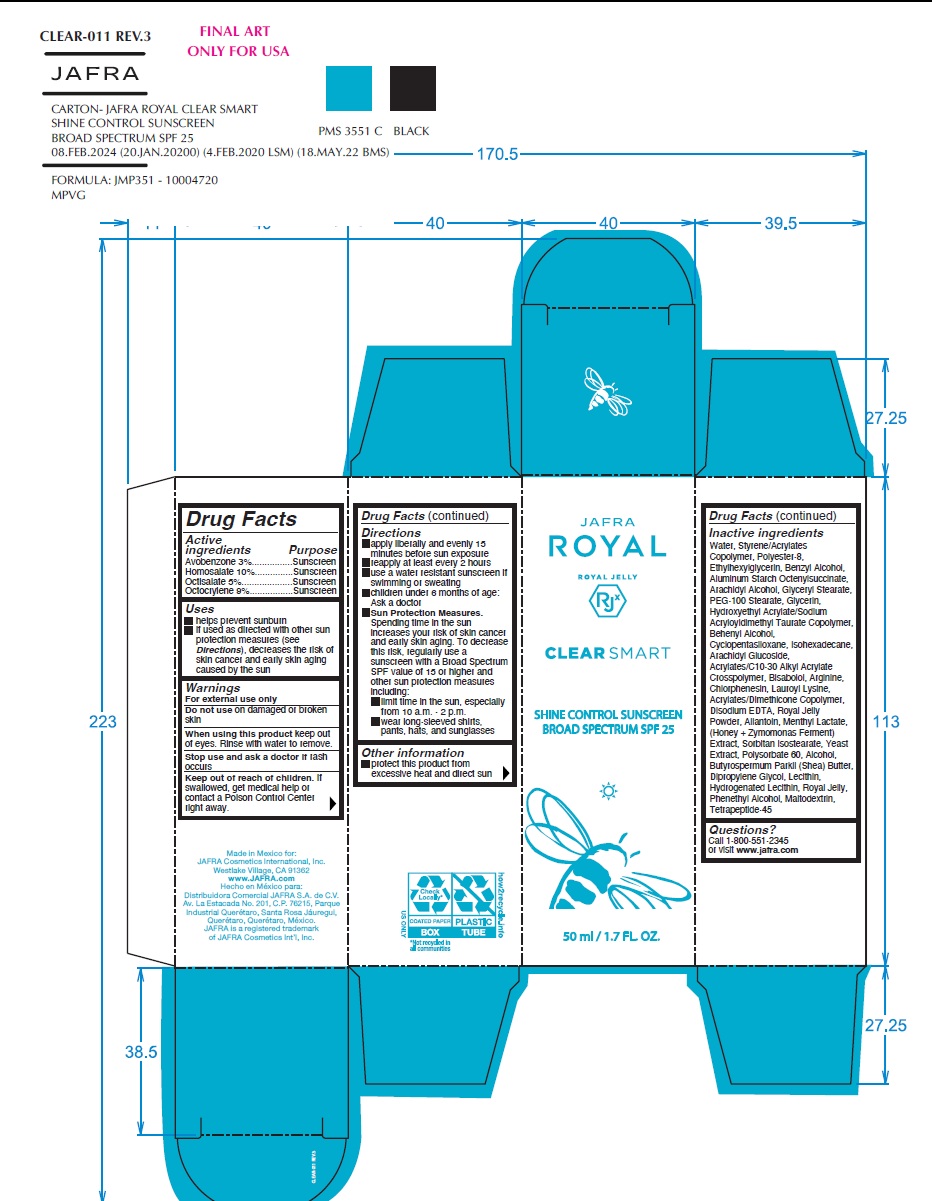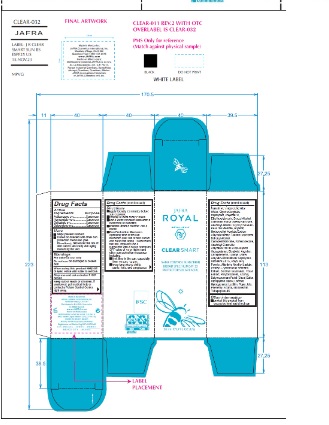 DRUG LABEL: Clear Smart Shine Control Sunscreen Broad Spectrum SPF 25
NDC: 68828-290 | Form: CREAM
Manufacturer: Distribuidora Comercial Jafra, S.A. de C.V.
Category: otc | Type: HUMAN OTC DRUG LABEL
Date: 20251105

ACTIVE INGREDIENTS: AVOBENZONE 3 g/100 mL; HOMOSALATE 10 g/100 mL; OCTISALATE 5 g/100 mL; OCTOCRYLENE 9 g/100 mL
INACTIVE INGREDIENTS: MENTHYL LACTATE, (-)-; ALLANTOIN; ARGININE; DOCOSANOL; ETHYLHEXYLGLYCERIN; LEVOMENOL; WATER; LECITHIN, SOYBEAN; SHEA BUTTER; GLYCERIN; CYCLOMETHICONE 5; POLYESTER-8 (1400 MW, CYANODIPHENYLPROPENOYL CAPPED); ISOHEXADECANE; GLYCERYL MONOSTEARATE; POLYSORBATE 60; BENZYL ALCOHOL; EDETATE DISODIUM; PEG-100 STEARATE; HONEY; HYDROXYETHYL ACRYLATE/SODIUM ACRYLOYLDIMETHYL TAURATE COPOLYMER (100000 MPA.S AT 1.5%); DIPROPYLENE GLYCOL; ROYAL JELLY; ALUMINUM STARCH OCTENYLSUCCINATE; ARACHIDYL ALCOHOL; ARACHIDYL GLUCOSIDE; HYDROGENATED SOYBEAN LECITHIN; MALTODEXTRIN; SORBITAN ISOSTEARATE; ALCOHOL; PHENYLETHYL ALCOHOL; CHLORPHENESIN; LAUROYL LYSINE; 2-ETHYLHEXYL ACRYLATE, METHACRYLATE, METHYL METHACRYLATE, OR BUTYL METHACRYLATE/HYDROXYPROPYL DIMETHICONE COPOLYMER (30000-300000 MW); YEAST, UNSPECIFIED; CARBOMER COPOLYMER TYPE B (ALLYL PENTAERYTHRITOL CROSSLINKED)

Clear Smart Shine Control Sunscreen Broad Spectrum SPF 25

Active Ingredients

Avobenzone 3%

Homosalate 10%

Octisalate 5%

Octocrylene 9%

Purpose

Sunscreen

Uses

- helps prevent sunburn
- if used as directed with other sun protection measures (see Directions), decreases the risk of skin cancer and early skin aging caused by the sun.

Warnings

For external use only

Do not use on damaged or broken skin
When using this product keep out of eyes. Rinse with water to remove.

Stop use and ask a doctor if rash occurs

Keep out of reach of children.If swallowed, get medical help or contact a Poison Control Center right away.

Directions

- Apply liberally and evenly 15 minutes before sun exposure
- Reapply at least every 2 hours
- Use a water resistant sunscreen if swimming or sweating
- Children under 6 months of age: Ask a doctor
- Sun Protection Measures.Spending time in the sun increases your risk of skin cancer and early skin aging. To decrease this risk, regularly use a sunscreen with a Broad Spectrum SPF value of 15 or higher and other sun protection measures including:

• limit time in the sun, especially from 10 a.m. – 2 p.m.

• wear long-sleeved shirts, pants, hats, and sunglasses

Other information

• protect this product from excessive heat and direct sun

Inactive ingredients

Water, Styrene/Acrylates Copolymer, Polyester-8, Ethylhexylglycerin, Benzyl Alcohol, Aluminum Starch Octenylsuccinate, Arachidyl Alcohol, Glyceryl Stearate, PEG-100 Stearate, Glycerin, Hydroxyethyl Acrylate/Sodium Acryloyldimethyl Taurate Copolymer, Behenyl Alcohol, Cyclopentasiloxane, Isohexadecane, Arachidyl Glucoside, Acrylates/C10-30 Alkyl Acrylate Crosspolymer, Bisabolol, Arginine, Chlorphenesin, Lauroyl Lysine, Acrylates/Dimethicone Copolymer, Disodium EDTA, Royal Jelly Powder, Allantoin, Menthyl Lactate, (Honey + Zymomonas Ferment) Extract, Sorbitan Isostearate, Yeast Extract, Polysorbate 60, Alcohol, Butyrospermum Parkii (Shea) Butter, Dipropylene Glycol, Lecithin, Hydrogenated Lecithin, Royal Jelly, Phenethyl Alcohol, Maltodextrin, Tetrapeptide-45

Questions?Call 1-800-551-2345 or visit www.jafra.com